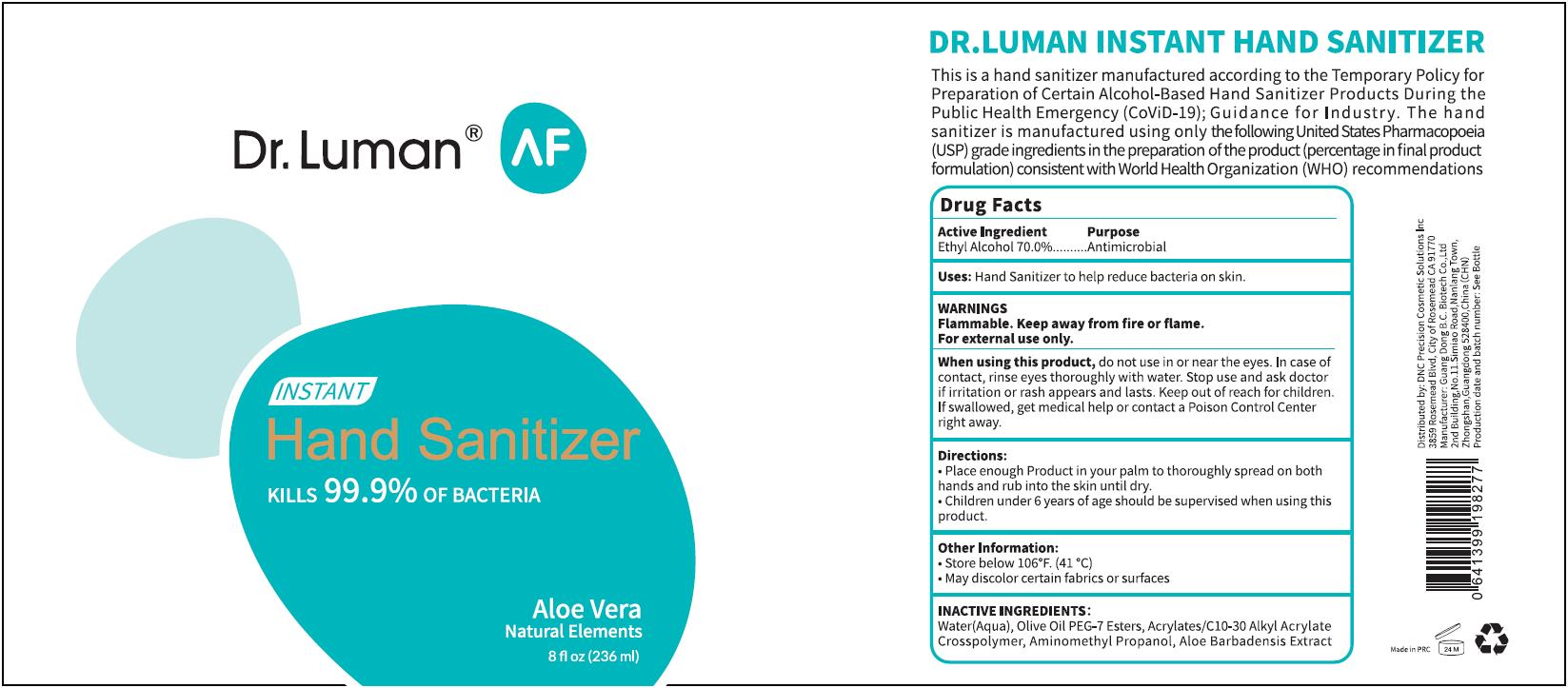 DRUG LABEL: Hand Sanitizer
NDC: 74738-1105 | Form: GEL
Manufacturer: GuangDong B.C. Biotech Co., Ltd.
Category: otc | Type: HUMAN OTC DRUG LABEL
Date: 20200507

ACTIVE INGREDIENTS: ALCOHOL 165.2 mL/236 mL
INACTIVE INGREDIENTS: PEG-7 STEARATE; CARBOMER INTERPOLYMER TYPE A (ALLYL SUCROSE CROSSLINKED); WATER; ALOE VERA LEAF; AMINOMETHYLPROPANOL

B.C., Hand Sanitizer, 70% Alcohol, Gel, N 236mL

Active Ingredient(s)

Ethyl Alcohol 70% v/v. Purpose: Antimicrobial

Purpose

Hand Sanitizer to help reduce bactreia on skin.

Use

Hand Sanitizer to help reduce bacteria on skin.

Warnings

Flammable. Keep away from fire or flame.

For external use only.

Do not use in or near the eyes.

In case of contact, rinse eyes thoroughly with water.

When using this product, do not use in or near the eyes.

Stop use and ask a doctor if irritation or rash appears and lasts.

Keep out of reach of children. If swallowed, get medical help or contact a Poison Control Center right away.

Directions

- Place enough Product in your palm to thoroughly spread on both hands and rub into the skin until dry.
- Children under 6 years of age should be supervised when using this product.

Other information

- Store below 106℉ (41℃)
- May discolor certain fabrics or surfaces

Inactive ingredients

Water (Aqua), Olive Oil PEG-7 Esters, Acrylates/C10-30 Alkyl, Acrylate Crosspolymer, Aminomethyl Propanol, Aloe Barbadensis Leaf Extract